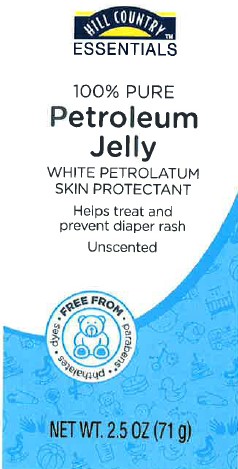 DRUG LABEL: Petroleum
NDC: 37808-960 | Form: JELLY
Manufacturer: H E B
Category: otc | Type: HUMAN OTC DRUG LABEL
Date: 20260224

ACTIVE INGREDIENTS: PETROLATUM 1 g/1 g

HEB 069 960.000/960AA
Baby Petroleum Jelly

Active ingredient

White Petrolatum, USP (100%)

Purpose

Skin Protectant

Use

- helps treat and prevent diaper rash
- protects chafed skin due to diaper rash
- helps seal out wetness

Warnings

For external use only

Do not use on

- deep or puncture wounds
- animal bites
- serious burns

When using this product

- do not get into eyes

Stop use and ask a doctor if

- condition worsens
- systems last longer than 7 days or clear up and occur again within a few days

Keep out of reach of children.

If swallowed, get medical help or contact a Poison Control Center right away.

Directions

- change wet and soiled diapers promptly
- cleanse the diaper area, and allow to dry
- apply product liberally as often as necessary, with each diaper change, and especially at bedtime or anytime when exposure to wet diapers may be prolonged

INACTIVE INGREDIENT

None

ADVERSE REACTIONS

WE HOPE YOU ARE SATISFIED WITH THIS PRODUCT.

IF NOT, WE WILL CHEERFULLY REFUND YOUR MONEY.

DISTRIBUTED BY: H-E-B

SAN ANTONIO, TX 78204

*This product would not normally contain parabens.

principal display panel

HILL COUNTRY ESSENTIALS

100% Pure

Petroleum Jelly

White Petrolatum

Skin Protectant

Helps treat and prevent diaper rash

Unscented

FREE FROM

- parabens
- phthalates
- dyes

NET WT 2.5 OZ (71 g)